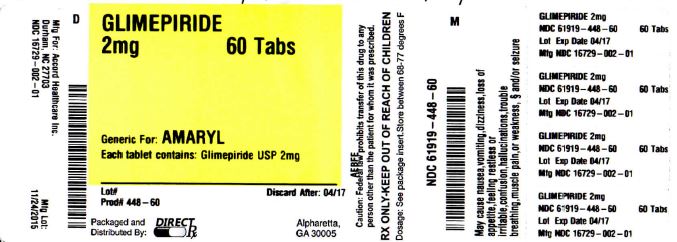 DRUG LABEL: GLIMEPIRIDE
NDC: 61919-448 | Form: TABLET
Manufacturer: DirectRX
Category: prescription | Type: HUMAN PRESCRIPTION DRUG LABEL
Date: 20151124

ACTIVE INGREDIENTS: GLIMEPIRIDE 2 mg/1 1
INACTIVE INGREDIENTS: FERRIC OXIDE YELLOW; FD&C BLUE NO. 2; LACTOSE MONOHYDRATE; SODIUM STARCH GLYCOLATE TYPE A POTATO; POVIDONE; MAGNESIUM STEARATE

GLIMEPIRIDE

Dosage and Administration

2.1 Recommended Dosing

Glimepiride tablets should be administered with breakfast or the first main meal of the day.

The recommended starting dose of glimepiride tablet is 1 mg or 2 mg once daily. Patients at increased risk for hypoglycemia (e.g., the elderly or patients with renal impairment) should be started on 1 mg once daily [see Warnings and Precautions (5.1) and Use in Specific Populations (8.5, 8.6)].

After reaching a daily dose of 2 mg, further dose increases can be made in increments of 1 mg or 2 mg based upon the patient’s glycemic response. Uptitration should not occur more frequently than every 1 to 2 weeks. A conservative titration scheme is recommended for patients at increased risk for hypoglycemia [see Warnings and Precautions (5.1) and Use in Specific Populations (8.5, 8.6)].

The maximum recommended dose is 8 mg once daily.

Patients being transferred to glimepiride from longer half-life sulfonylureas (e.g., chlorpropamide) may have overlapping drug effect for 1 to 2 weeks and should be appropriately monitored for hypoglycemia.

When colesevelam is coadministered with glimepiride, maximum plasma concentration and total exposure to glimepiride is reduced. Therefore, glimepiride should be administered at least 4 hours prior to colesevelam.

Dosage Forms and Strengths

Glimepiride tablet is formulated as tablets of:

1 mg tablets (pink coloured, oval shaped, biconvex, uncoated tablets debossed with ‘AHI 1’ on one side and break line on the other)
2 mg tablets (green coloured, oval shaped, biconvex, uncoated tablets debossed with ‘AHI 2’ on one side and break line on the other)
4 mg tablets (blue coloured, oval shaped, biconvex, uncoated tablets debossed with ‘AHI 4’ on one side and break line on the other)

Contraindications

Glimepiride tablet is contraindicated in patients with a history of a hypersensitivity reaction to:

Glimepiride or any of the product’s ingredients [see Warnings and Precautions (5.2)].

Sulfonamide derivatives: Patients who have developed an allergic reaction to sulfonamide derivatives may develop an allergic reaction to glimepiride. Do not use glimepiride in patients who have a history of an allergic reaction to sulfonamide derivatives.

Reported hypersensitivity reactions include cutaneous eruptions with or without pruritus as well as more serious reactions (e.g. anaphylaxis, angioedema, Stevens-Johnson Syndrome, dyspnea) [see Warnings and Precautions (5.2) and Adverse Reactions (6.2)].

Adverse Reactions

The following serious adverse reactions are discussed in more detail below and elsewhere in the labeling:

Hypoglycemia [see Warnings and Precautions (5.1) ]
Hemolytic anemia [see Warnings and Precautions (5.3) ]

In clinical trials, the most common adverse reactions with glimepiride were hypoglycemia, dizziness, asthenia, headache, and nausea.

6.1 Clinical Trials Experience

Because clinical trials are conducted under widely varying conditions, adverse reaction rates observed in the clinical trials of a drug cannot be directly compared to rates in the clinical trials of another drug and may not reflect the rates observed in practice. Approximately 2,800 patients with type 2 diabetes have been treated with glimepiride in the controlled clinical trials. In these trials, approximately 1,700 patients were treated with glimepiride for at least 1 year.

Table 1 summarizes adverse events, other than hypoglycemia, that were reported in 11 pooled placebo-controlled trials, whether or not considered to be possibly or probably related to study medication. Treatment duration ranged from 13 weeks to 12 months. Terms that are reported represent those that occurred at an incidence of ≥5% among glimepiride-treated patients and more commonly than in patients who received placebo.

Hypoglycemia:

In a randomized, double-blind, placebo-controlled monotherapy trial of 14 weeks duration, patients already on sulfonylurea therapy underwent a 3-week washout period then were randomized to glimepiride 1 mg, 4 mg, 8 mg or placebo. Patients randomized to glimepiride 4 mg or 8 mg underwent forced-titration from an initial dose of 1 mg to these final doses, as tolerated [see Clinical Studies (14.1)]. The overall incidence of possible hypoglycemia (defined by the presence of at least one symptom that the investigator believed might be related to hypoglycemia; a concurrent glucose measurement was not required) was 4% for glimepiride 1 mg, 17% for glimepiride 4 mg, 16% for glimepiride 8 mg and 0% for placebo. All of these events were self-treated.

In a randomized, double-blind, placebo-controlled monotherapy trial of 22 weeks duration, patients received a starting dose of either 1 mg glimepiride or placebo daily. The dose of glimepiride was titrated to a target fasting plasma glucose of 90 to 150 mg/dL. Final daily doses of glimepiride were 1, 2, 3, 4, 6 or 8 mg [see Clinical Studies (14.1)]. The overall incidence of possible hypoglycemia (as defined above for the 14-week trial) for glimepiride vs. placebo was 19.7% vs. 3.2%. All of these events were self-treated.

Weight gain: glimepiride, like all sulfonylureas, can cause weight gain [see Clinical Studies (14.1)].

Allergic Reactions: In clinical trials, allergic reactions, such as pruritus, erythema, urticaria, and morbilliform or maculopapular eruptions, occurred in less than 1% of glimepiride- treated patients. These may resolve despite continued treatment with glimepiride. There are postmarketing reports of more serious allergic reactions (e.g., dyspnea, hypotension, shock) [see Warnings and Precautions (5.2)].

Laboratory Tests:
Elevated Serum Alanine Aminotransferase (ALT):): In 11 pooled placebo-controlled trials of glimepiride, 1.9% of glimepiride-treated patients and 0.8% of placebo-treated patients developed serum ALT greater than 2 times the upper limit of the reference range.

6.2 Postmarketing Experience

The following adverse reactions have been identified during post-approval use of glimepiride. Because these reactions are reported voluntarily from a population of uncertain size, it is not always possible to reliably estimate their frequency or establish a causal relationship to drug exposure.

Serious hypersensitivity reactions, including anaphylaxis, angioedema, and Stevens-Johnson Syndrome [see Warnings and Precautions (5.2)]
Hemolytic anemia in patients with and without G6PD deficiency [see Warnings and Precautions (5.3)]
Impairment of liver function (e.g. with cholestasis and jaundice), as well as hepatitis, which may progress to liver failure.
Porphyria cutanea tarda, photosensitivity reactions and allergic vasculitis
Leukopenia, agranulocytosis, aplastic anemia, and pancytopenia
Thrombocytopenia (including severe cases with platelet count less than 10,000/μL) and thrombocytopenic purpura
Hepatic porphyria reactions and disulfiram-like reactions
Hyponatremia and syndrome of inappropriate antidiuretic hormone secretion (SIADH), most often in patients who are on other medications or who have medical conditions known to cause hyponatremia or increase release of antidiuretic hormone

- to report suspected adverse reactions call 1-800-332-1088 [to report suspected adverse reactions call 1-800-332-1088]